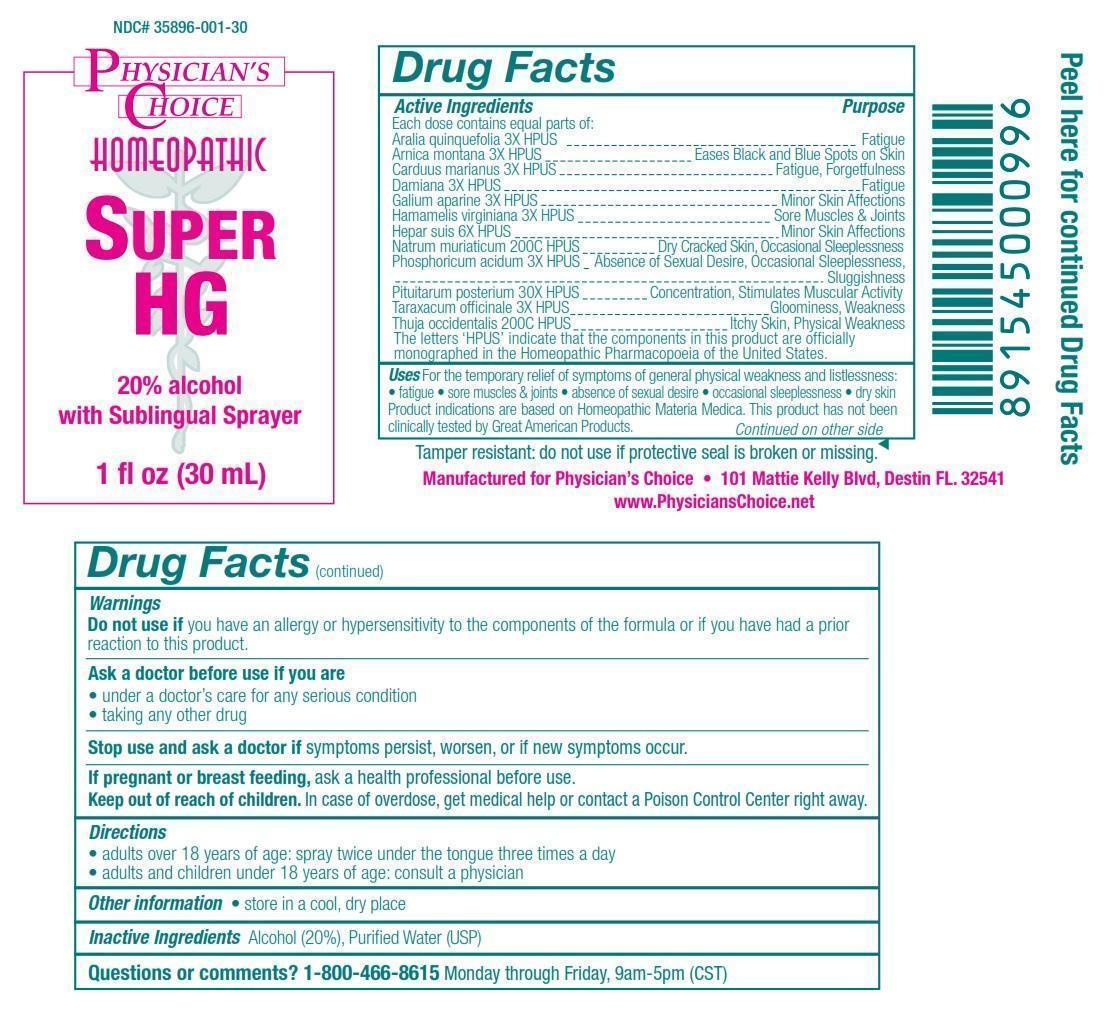 DRUG LABEL: Super HG
                
NDC: 35896-001 | Form: LIQUID
Manufacturer: Physician's Choice, Inc.
Category: homeopathic | Type: HUMAN OTC DRUG LABEL
Date: 20130426

ACTIVE INGREDIENTS: AMERICAN GINSENG 3 [hp_X]/30 mL; ARNICA MONTANA 3 [hp_X]/30 mL; SILYBUM MARIANUM SEED 3 [hp_X]/30 mL; TURNERA DIFFUSA LEAFY TWIG 3 [hp_X]/30 mL; GALIUM APARINE 3 [hp_X]/30 mL; HAMAMELIS VIRGINIANA ROOT BARK/STEM BARK 3 [hp_X]/30 mL; PORK LIVER 6 [hp_X]/30 mL; SODIUM CHLORIDE 200 [hp_C]/30 mL; PHOSPHORIC ACID 3 [hp_X]/30 mL; SUS SCROFA PITUITARY GLAND 30 [hp_X]/30 mL; TARAXACUM OFFICINALE 3 [hp_X]/30 mL; THUJA OCCIDENTALIS LEAFY TWIG 200 [hp_C]/30 mL
INACTIVE INGREDIENTS: ALCOHOL; WATER

Drug Facts

Active Ingredients

Each dose contains equal parts of:

Aralia quinquefolia 3X HPUS

Arnica montana 3X HPUS

Carduus marianus 3X HPUS

Damiana 3X HPUS

Galium aparine 3X HPUS

Hamamelis virginiana 3X HPUS

Hepar suis 6X HPUS

Natrum muriaticum 200C HPUS

Phosphoricum acidum 3X HPUS

Pituitarum posterium 30X HPUS

Taraxacum officinale 3X HPUS

Thuja occidentalis 200C HPUS

The letters 'HPUS' indicate that the components in this product are officially monographed in the Homeopathic Pharmacopoeia of the United States.

Purpose

Aralia quinquefolia 3X HPUS......................Fatigue
Arnica montana 3X HPUS..........................Eases Black and Blue Spots on Skin
Carduus marianus 3X HPUS.......................Fatigue, Forgetfulness
Damiana 3X HPUS....................................Fatigue
Galium aparine 3X HPUS...........................Minor Skin Affections
Hamamelis virginiana 3X HPUS.................Sore Muscles and Joints
Hepar suis 6X HPUS................................Minor Skin Affections
Natrum muriaticum 200C HPUS................Dry Cracked Skin, Occasional Sleeplessness
Phosphoricum acidum 3X HPUS...............Absence of Sexual Desire, Occasional Sleeplessness, Sluggishness
Pituitarum posterium 30X HPUS...............Concentration, Stimulates Muscular Activity
Taraxacum officinale 3X HPUS.................Gloominess, Weakness
Thuja occidentalis 200C HPUS..................Itchy Skin, Physical Weakness

Uses

For the temporary relief of symptoms of general physical weakness and listlessness:

- fatigue
- sore muscles and joints
- absence of sexual desire
- occasional sleeplessness
- dry skin

Product indications are based on Homeopathic Materia Medica. This product has not been clinically tested by Great American Products.

Warnings

Do not use if you have an allergy or hypersensitivity to the components of the formula or if you have had a prior reaction to this product.

Ask a doctor before use if you are

- under a doctor's care for any serious condition
- taking any other drug

Stop use and ask a doctor if symptoms persist, worsen, or if new symptoms occur.

PREGNANCY OR BREAST FEEDING

If pregnant or breast feeding, ask a health professional before use.

Keep out of reach of children.

OTHER SAFETY INFORMATION

In case of overdose, get medical help or contact a Poison Control Center right away.

Directions

- adults over 18 years of age: spray twice under the tongue three times a day
- adults and children under 18 years of age: consult a physician

Other information

- store in a cool, dry place

Inactive Ingredients

Alcohol (20%), Purified Water (USP)

Questions or comments?

1-800-466-8615 Monday through Friday, 9am - 5pm (CST)

DESCRIPTION

Tamper resistant: do not use if protective seal is broken or missing.

Manufactured for Physician's Choice

101 Mattie Kelly Bldv, Destin FL. 32541

www.PhysiciansChoice.net

Peel here for continued Drug Facts

Principal Display Panel

NDC# 35896-001-30

PHYSICIAN'S CHOICE

HOMEOPATHIC

SUPER HG

20% alcohol with Sublingual Sprayer

1 fl oz (30 mL)